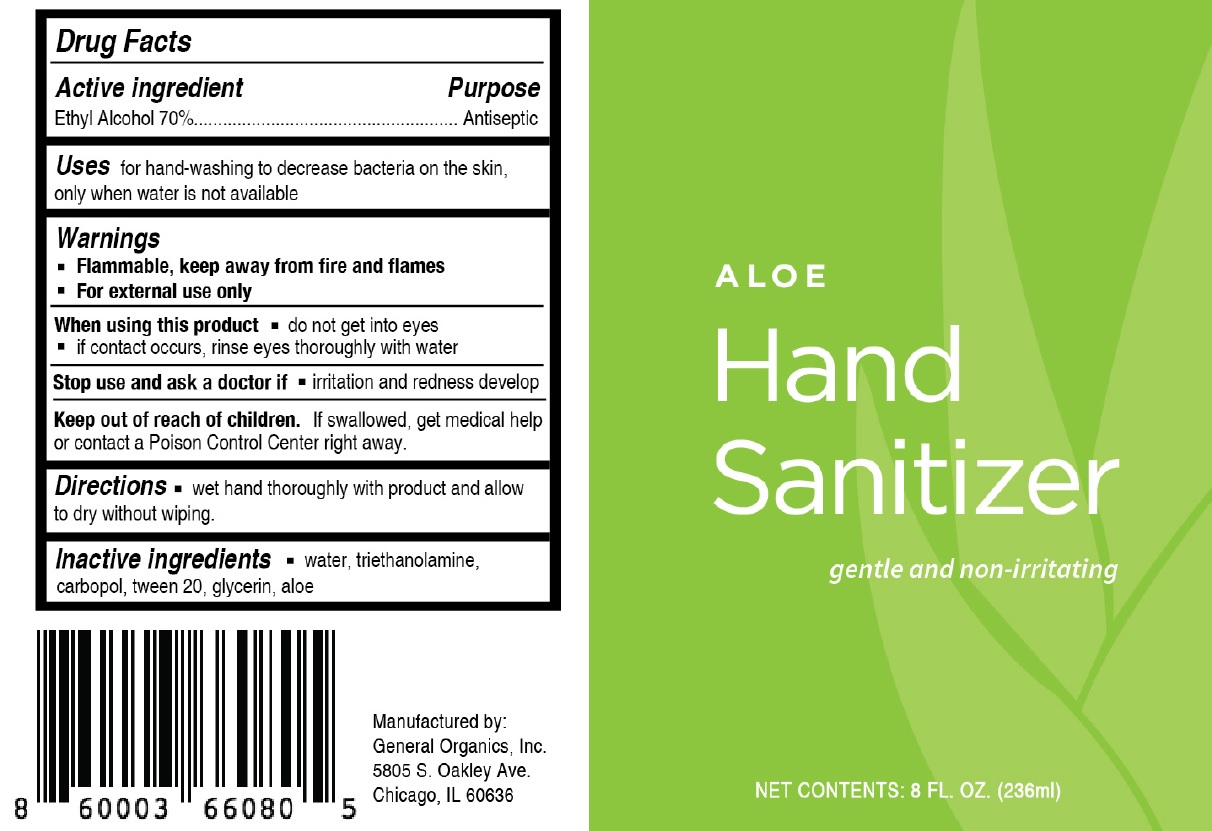 DRUG LABEL: Hand Sanitizer
NDC: 76924-000 | Form: GEL
Manufacturer: General Organics Inc.
Category: otc | Type: HUMAN OTC DRUG LABEL
Date: 20240520

ACTIVE INGREDIENTS: ALCOHOL 0.7 mL/1 mL
INACTIVE INGREDIENTS: WATER; TROLAMINE; CARBOMER HOMOPOLYMER, UNSPECIFIED TYPE; POLYSORBATE 20; GLYCERIN; ALOE

Hand Sanitizer

Active ingredient

Ethyl Alcohol 70%

Purpose

Antiseptic

Uses

for hand-washing to decrease bacteria on the skin, only when water is not available

Warnings

- Flammable, keep away from fire and flames
- For external use ony

When using this product

- do not get into eyes
- if contact occurs, rinse eyes thoroughly with water

Stop use and ask a doctor if

- irritation and redness develop

Keep out of reach of children.

If swallowed, get medical help or contact a Poison Control Cente right away.

Directions

- wet hand thoroughly with product and allow to dry without wiping.

Inactive ingredients

water, triethanolamine, carbopol, tween 20, glycerin, aloe